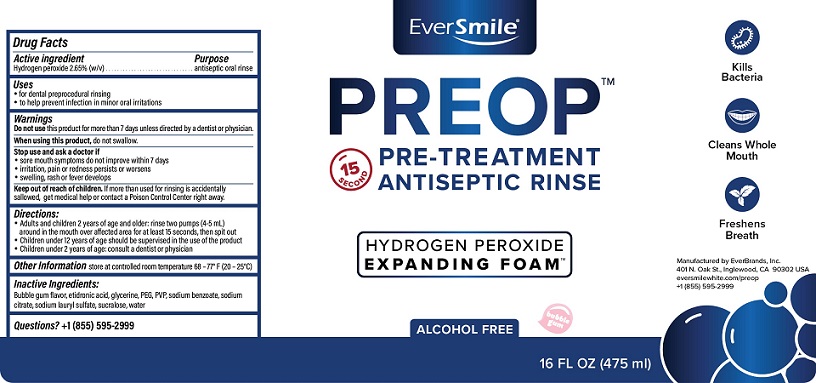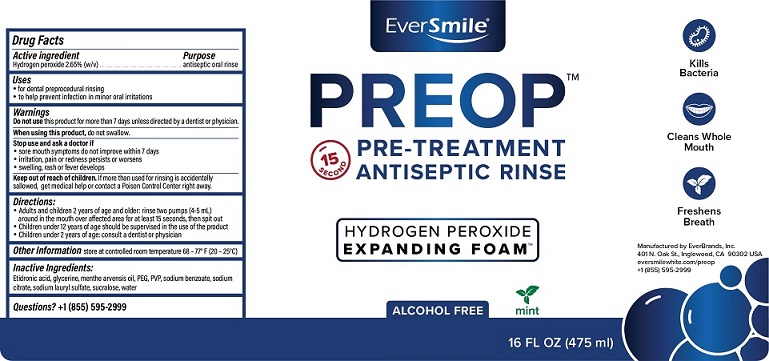 DRUG LABEL: PREOP
NDC: 72655-200 | Form: RINSE
Manufacturer: Everbrands, Inc.
Category: otc | Type: HUMAN OTC DRUG LABEL
Date: 20210308

ACTIVE INGREDIENTS: HYDROGEN PEROXIDE 26.5 mg/1 mL
INACTIVE INGREDIENTS: ETIDRONIC ACID; GLYCERIN; MENTHA ARVENSIS FLOWER OIL; POLYETHYLENE GLYCOL, UNSPECIFIED; POVIDONE, UNSPECIFIED; SODIUM BENZOATE; SODIUM CITRATE; SODIUM LAURETH SULFATE; SUCRALOSE; WATER

PREOP Pre-Treatment Antiseptic Rinse

DRUG FACTS

Active ingredient

Hydrogen Peroxide 2.65%

Purpose

antiseptic oral rinse

Uses

- for dental procedural rinsing
- to help prevent infection in minor oral irritations

Warnings

Do not use this product for more than 7 days unless directed by a dentist or physician.

When using this product, do not swallow

Stop use and ask a doctor if

- sore mouth symptoms do not improve within 7 days
- irritations, pain or redness persists or worsens
- swelling, rash or fever develops

Keep out of reach of children. If more than used for rinsing is accidentally

swallowed, get medical help or contact a poison Control Center right away.

Directions:
• Adults and children 2 years of age and older: rinse two pumps (4-5 mL)
around in the mouth over the affected area for at least 15 seconds, then spit out
• Children under 12 years of age should be supervised in the use of this product
• Children under 2 years of age: consult a dentist or physician

OTHER SAFETY INFORMATION

Other Informationstore at controlled room temperature 68-77°F (20 - 25°C)

Inactive Ingredients:

Etidronic acid, glycerine, menthe arvensis oil, PEG, PVP, sodium benzoate, sodium

citrate, sodium lauryl sulfate, sucralose, water

Questions? +1 (855) 595-2999

PACKAGE LABEL

EverSmile

PREOP™

PRE-TREATMENT

ANTISEPTIC RINSE

HYDROGEN PEROXIDE

EXPANDING FOAM

16 FL OZ (475 mL)

Manufactured by EverBrands, Inc

401 N. Oak St., Inglewood, CA 90302

eversmilewhite.com/preop

+1 (855) 595-2999

Mint

Bubble Gum

res